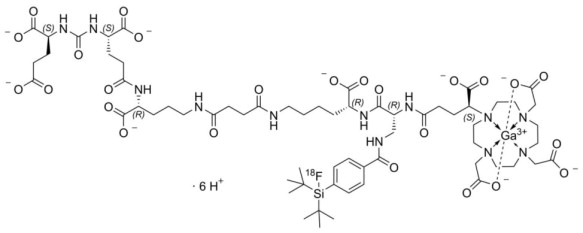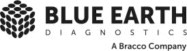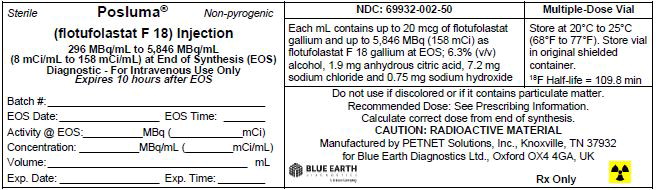 DRUG LABEL: POSLUMA
NDC: 69932-002 | Form: INJECTION
Manufacturer: Blue Earth Diagnostics
Category: prescription | Type: HUMAN PRESCRIPTION DRUG LABEL
Date: 20250924

ACTIVE INGREDIENTS: FLOTUFOLASTAT F-18 158 mCi/1 mL
INACTIVE INGREDIENTS: SODIUM HYDROXIDE; WATER; SODIUM CHLORIDE; CITRIC ACID MONOHYDRATE

HIGHLIGHTS OF PRESCRIBING INFORMATION

These highlights do not include all the information needed to use POSLUMA® safely and effectively. See full prescribing information for POSLUMA.
POSLUMA (flotufolastat F 18) injection, for intravenous use
Initial U.S. Approval: 2023

1 INDICATIONS AND USAGE

POSLUMA is a radioactive diagnostic agent indicated for positron emission tomography (PET) of prostate-specific membrane antigen (PSMA) positive lesions in men with prostate cancer:

- with suspected metastasis who are candidates for initial definitive therapy
- with suspected recurrence based on elevated serum prostate-specific antigen (PSA) level. (1)

2 DOSAGE AND ADMINISTRATION

- Recommended amount of radioactivity of POSLUMA is 296 MBq (8 mCi) administered as an intravenous bolus injection. (2.2)
- Initiate imaging approximately 60 minutes after administration. Scanning should start from mid-thigh and proceed to base of skull. (2.4)
- See full prescribing information for additional preparation, handling, administration, imaging, and radiation dosimetry information. (2.3, 2.4)

3 DOSAGE FORMS AND STRENGTHS

Injection: 296 MBq/mL to 5,846 MBq/mL (8 mCi/mL to 158 mCi/mL) as flotufolastat F 18 gallium in approximately 25 mL at end of synthesis in a multiple-dose vial. (3)

4 CONTRAINDICATIONS

None. (4)

5 WARNINGS AND PRECAUTIONS

- Risk of Image Misinterpretation: Image interpretation errors can occur with POSLUMA imaging. Interpretation of POSLUMA PET may differ depending on imaging readers in patients with suspected recurrence of prostate cancer. Consider multidisciplinary consultation and histopathological confirmation. (5.1, 14.2)
- Radiation risk: POSLUMA contributes to a patient's long-term cumulative radiation exposure. Ensure safe handling to protect patients and health care workers from unintentional radiation exposure. (2.1, 5.2)

6 ADVERSE REACTIONS

The most common adverse reactions (≥0.4%) are diarrhea, blood pressure increase, and injection site pain. (6.1)

To report SUSPECTED ADVERSE REACTIONS, contact Blue Earth Diagnostics Ltd at 1-844-POSLUMA (1-844-767-5862) or FDA at 1-800-FDA-1088 or www.fda.gov/medwatch.

FULL PRESCRIBING INFORMATION

1 INDICATIONS AND USAGE

POSLUMA is indicated for positron emission tomography (PET) of prostate-specific membrane antigen (PSMA) positive lesions in men with prostate cancer

- with suspected metastasis who are candidates for initial definitive therapy.
- with suspected recurrence based on elevated serum prostate-specific antigen (PSA) level.

2 DOSAGE AND ADMINISTRATION

2.1 Radiation Safety - Drug Handling

Handle POSLUMA with safety measures to minimize radiation exposure [see Warnings and Precautions (5.2)] . Use waterproof gloves, effective radiation shielding, including syringe shields, and other appropriate safety measures when handling and administering POSLUMA.

Radiopharmaceuticals should be used by or under the control of physicians who are qualified by specific training and experience in the safe use and handling of radionuclides, and whose experience and training have been approved by the appropriate governmental agency authorized to license the use of radionuclides.

2.2 Recommended Dose and Administration Instructions

Recommended Dose

The recommended amount of radioactivity to be administered in adults is 296 MBq (8 mCi) as an intravenous bolus injection.

Preparation and Administration Instructions

- Inspect POSLUMA visually for particulate matter and discoloration before administration. Do not use the drug if the solution contains particulate matter or is discolored.
- Use aseptic technique and radiation shielding when withdrawing and administering POSLUMA.
- Calculate the necessary volume to administer based on calibration time and required dose.
- The recommended maximum volume of undiluted POSLUMA is 5 mL.
- POSLUMA may be diluted with 0.9% Sodium Chloride Injection, USP.
- Assay the dose in a dose calibrator before administration.

Post Administration Instructions

- After the POSLUMA injection, administer an intravenous flush of sterile 0.9% Sodium Chloride Injection, USP to ensure full delivery of the dose.
- Dispose of any unused drug in a safe manner in compliance with applicable regulations.

2.3 Patient Preparation

Instruct patients to drink water prior to administration of POSLUMA to ensure adequate hydration and to continue drinking and voiding frequently for the first few hours following administration to reduce radiation exposure.

2.4 Image Acquisition

- Patients should void immediately prior to imaging.
- Position the patient supine with arms above the head.
- Begin image acquisition approximately 60 minutes after POSLUMA injection.
- Image acquisition should start from mid-thigh and proceed to the base of the skull.
- Scan duration is approximately 20 minutes depending on the number of bed positions and acquisition time per bed position (typically 3 minutes). Adapt imaging technique according to the equipment used and patient characteristics in order to obtain the best image quality possible.

2.5 Image Display and Interpretation

POSLUMA binds to PSMA. PET images obtained using POSLUMA indicate the presence of PSMA in tissues [see Clinical Pharmacology (12.1)] . Lesions should be considered suspicious if uptake is greater than physiologic uptake in that tissue or greater than adjacent background if no physiologic uptake is expected. Tumors that do not express PSMA will not be visualized. Increased uptake in tumors is not specific for prostate cancer [see Warnings and Precautions (5.1)].

2.6 Radiation Dosimetry

Estimated absorbed radiation doses for adult patients following intravenous injection of POSLUMA are shown in Table 1. The effective radiation dose resulting from the administration of the recommended activity of 296 MBq of POSLUMA is 4.1 mSv. The radiation absorbed doses to the critical organs of adrenal glands, kidneys, and submandibular glands for the recommended activity of 296 MBq are 54.3 mGy, 51 mGy, and 43.8 mGy, respectively. When PET/CT is performed, exposure to radiation will increase by an amount dependent on the settings used in the CT acquisition.

Table 1: Estimated Radiation Absorbed Doses in Organs/Tissues in Adults who Received POSLUMA
Organ/Tissue | Absorbed Dose per Unit Administered Activity (mGy/MBq)
 | Mean
Adrenal glands | 0.184
Brain | 0.002
Breasts | 0.004
Gallbladder wall | 0.017
Lower large intestine wall | 0.007
Upper large intestine wall | 0.01
Heart wall | 0.02
Kidneys | 0.172
Lacrimal glands | 0.08*
Liver | 0.062
Lungs | 0.01
Muscle | 0.006
Osteogenic cells | 0.012
Ovaries | 0.005
Pancreas | 0.028
Parotid glands | 0.114*
Red bone marrow | 0.01
Skin | 0.002
Small intestine | 0.012
Spleen | 0.083
Stomach wall | 0.012
Sublingual glands | 0.065*
Submandibular glands | 0.148*
Testes | 0.005
Thymus gland | 0.01
Thyroid | 0.01
Urinary bladder wall | 0.006**
Uterus | 0.011
Effective dose (mSv/MBq) | 0.014**
*The absorbed dose value reflects self-irradiation only; no dose contribution from other regions to the glands is added.**A 1-hour bladder voiding interval is assumed.

3 DOSAGE FORMS AND STRENGTHS

Injection: 296 MBq/mL to 5,846 MBq/mL (8 mCi/mL to 158 mCi/mL) as flotufolastat F 18 gallium in approximately 25 mL at end of synthesis supplied as a clear, colorless solution in a multiple-dose vial.

4 CONTRAINDICATIONS

None.

5 WARNINGS AND PRECAUTIONS

5.1 Risk of Image Misinterpretation

Image interpretation errors can occur with POSLUMA PET. A negative image does not rule out the presence of prostate cancer and a positive image does not confirm the presence of prostate cancer. The performance of POSLUMA for imaging metastatic pelvic lymph nodes in patients prior to initial definitive therapy seems to be affected by serum PSA levels and risk grouping [See Clinical Studies (14.1)] . The performance of POSLUMA for imaging patients with biochemical evidence of recurrence of prostate cancer seems to be affected by serum PSA levels [See Clinical Studies (14.2)] . Flotufolastat F 18 uptake is not specific for prostate cancer and may occur in other types of cancer, in non-malignant processes, and in normal tissues. Clinical correlation, which may include histopathological evaluation, is recommended.

Risk of Image Misinterpretation in Patients with Suspected Prostate Cancer Recurrence

The interpretation of POSLUMA PET may differ depending on imaging readers, particularly in the prostate/prostate bed region [see Clinical Studies (14.2)]. Because of the associated risk of false positive interpretation, consider multidisciplinary consultation and histopathological confirmation when clinical decision-making hinges on flotufolastat F18 uptake only in the prostate/prostate bed region or only on uptake interpreted as borderline.

5.2 Radiation Risks

POSLUMA use contributes to a patient's overall long-term cumulative radiation exposure. Long-term cumulative radiation exposure is associated with an increased risk for cancer. Advise patients to hydrate before and after administration and to void frequently after administration. Ensure safe handling to minimize radiation exposure to the patient and health care providers [see Dosage and Administration (2.1, 2.2)] .

6 ADVERSE REACTIONS

6.1 Clinical Trials Experience

Because clinical trials are conducted under widely varying conditions, adverse reaction rates observed in the clinical trials of a drug cannot be directly compared to rates in the clinical trials of another drug and may not reflect the rates observed in practice.

The safety of POSLUMA was evaluated in 747 patients with prostate cancer [see Clinical Studies (14.1, 14.2)] . All patients received a single administration of POSLUMA with an administered radioactivity (mean ± SD) of 307 ± 23 MBq (8.3 ± 0.6 mCi). The mean age of patients was 67 years (range: 43 to 86 years); distribution by race was 78% White, 12% Black or African American, 2% other, and 7% unreported; and distribution by ethnicity was 5% Hispanic/Latino, 87% non-Hispanic/Latino, and 8% unreported.

The adverse reactions reported in ≥ 0.4% of patients are shown in Table 2.

Table 2: Adverse Reactions in ≥ 0.4% of Patients with Prostate Cancer Receiving POSLUMA
Adverse Reaction | POSLUMA N = 747 n (%)
Diarrhea | 5 (0.7%)
Blood pressure increase | 4 (0.5%)
Injection site pain | 3 (0.4%)

7 DRUG INTERACTIONS

Androgen deprivation therapy (ADT) and other therapies targeting the androgen pathway, such as androgen receptor antagonists, can result in changes in uptake of flotufolastat F 18 in prostate cancer. The effect of these therapies on performance of POSLUMA PET has not been established.

8 USE IN SPECIFIC POPULATIONS

8.1 Pregnancy

Risk Summary

POSLUMA is not indicated for use in females. There are no available data on the use of POSLUMA in pregnant women to evaluate for a drug-associated risk of major birth defects, miscarriage, or adverse maternal or fetal outcomes. Animal reproduction studies have not been conducted with flotufolastat F 18. Radioactive drugs, including POSLUMA, have the potential to cause fetal harm depending on the fetal stage of development and the magnitude of the radiation dose.

8.2 Lactation

Risk Summary

POSLUMA is not indicated for use in females. There are no data on the presence of flotufolastat F 18 in human milk, the effect on the breastfed infant, or the effect on milk production.

8.4 Pediatric Use

The safety and effectiveness of POSLUMA have not been established in pediatric patients.

8.5 Geriatric Use

Among the total number of patients receiving POSLUMA in clinical studies of prostate cancer, 463 (62%) were 65 years of age and older, while 118 (16%) were 75 years of age and older [see Clinical Studies (14.1, 14.2)] . No overall differences in safety or effectiveness were observed between these patients and younger adult patients.

11 DESCRIPTION

11.1 Chemical Characteristics

POSLUMA (flotufolastat F 18) injection is a radioactive diagnostic agent for intravenous use. The active ingredient of POSLUMA is flotufolastat F 18 gallium, of which the molecular structure includes a DOTAGA complex with nonradioactive gallium. Radioactive fluorine-18 is covalently bound to silicon.

Chemically, flotufolastat F 18 gallium is gallate(6-), [(4 S,8 S,13 R,27 R,30 R,35 S)-35-[4,10-bis[(carboxy-k O)methyl]-7-(carboxymethyl)-1,4,7,10-tetraazacyclododec-1-yl-k N^1,k N^4,k N^7,k N^10]-30-[[[4-[bis(1,1-dimethylethyl)fluoro- ^18 F-silyl]benzoyl]amino]methyl]-1,36-dihydroxy-1,6,11,18,21,29,32,36-octaoxo-5,7,12,17,22,28,31-heptaazahexatriacontane-4,8,13,27-tetracarboxylato(9-)]-, hydrogen (1:6). The molecular weight is 1537.3 g/mol and the structural formula is:

POSLUMA is a sterile, non-pyrogenic, clear, colorless, and isotonic solution. Each mL contains up to 20 mcg of flotufolastat gallium, up to 5,846 MBq (158 mCi) as flotufolastat F 18 gallium at end of synthesis, and the following inactive ingredients: 6.3% (v/v) alcohol, 1.9 mg anhydrous citric acid, 7.2 mg sodium chloride, and 0.75 mg sodium hydroxide to adjust pH between 4 and 6. POSLUMA contains no preservative.

11.2 Physical Characteristics

POSLUMA contains fluorine-18 (F 18) which is a cyclotron produced radionuclide that decays by positron emission (β+ decay, 96.7%) and orbital electron capture (3.3%) to stable oxygen-18 with a physical half-life of 109.8 minutes (Table 3). The principal photons useful for diagnostic imaging are the coincident pair of 511 keV gamma photons, resulting from the interaction of the emitted positron with an electron (Table 4).

Table 3: Physical Decay Chart for Fluorine-18
Minutes | Fraction Remaining
0 | 1
15 | 0.909
30 | 0.826
60 | 0.683
110 | 0.5
220 | 0.25

Table 4: Principal Radiation Produced from Decay of Fluorine-18
 | Energy (keV) | Abundance (%)
Positron | 249.8 | 96.7
Gamma | 511 | 193.5

11.3 External Radiation

The point source air-kerma coefficient for F 18 is 3.75 × 10^-17 Gy m^2/(Bq s). The first half-value thickness of lead (Pb) for F 18 gamma rays is approximately 6 mm. The relative reduction of radiation emitted by F 18 that results from various thicknesses of lead shielding is shown in Table 5. The use of 8 cm of Pb will decrease the radiation transmission (i.e., exposure) by a factor of about 10,000.

Table 5: Radiation Attenuation of 511 keV Gamma Rays by Lead Shielding
Shield Thickness cm of Lead (Pb) | Coefficient of Attenuation
0.6 | 0.5
2 | 0.1
4 | 0.01
6 | 0.001
8 | 0.0001

10 OVERDOSAGE

In the event of an overdose of POSLUMA, maintain hydration of the patient and frequent voiding to minimize radiation exposure. A diuretic might also be considered. If possible, an estimate of the radiation effective dose administered to the patient should be made.

12 CLINICAL PHARMACOLOGY

12.1 Mechanism of action

Flotufolastat F 18 binds to PSMA (IC50 = 4.4 nM) expressed on cells, including prostate cancer cells, and is internalized. Prostate cancer cells usually overexpress PSMA. Fluorine-18 is a ß+ emitting radionuclide that can be detected using positron emission tomography.

12.2 Pharmacodynamics

The relationship between flotufolastat F 18 plasma concentrations and image interpretation has not been fully characterized.

12.3 Pharmacokinetics

Distribution

Following intravenous administration, flotufolastat F 18 distributes to liver (15.8% of administered activity), heart blood pool (7.4%), and kidneys (3.2%) and is cleared from the blood.

Elimination

Metabolism

Flotufolastat F 18 does not undergo metabolism up to 50 minutes post injection.

Excretion

Elimination is by urinary excretion. Approximately 7% of the administered activity was excreted in the urine in the first 2 hours post-injection with approximately 15% excreted by 4.5 hours post-injection.

13 NONCLINICAL TOXICOLOGY

13.1 Carcinogenesis, Mutagenesis, Impairment of Fertility

Animal studies to assess the carcinogenicity or mutagenic potential of flotufolastat have not been conducted. However, flotufolastat F 18 has the potential to be mutagenic because of the F 18 radionuclide.

No studies in animals have been performed to evaluate potential impairment of fertility in males or females.

14 CLINICAL STUDIES

14.1 Imaging Prior to Initial Definitive Therapy of Prostate Cancer

The safety and efficacy of POSLUMA were evaluated in LIGHTHOUSE (NCT04186819), a prospective, multicenter, open-label, single-arm study in patients with prostate cancer who were candidates for initial definitive therapy.

The study enrolled 356 patients diagnosed with unfavorable intermediate-risk (32%) or high-/very high-risk prostate cancer (68%) who were candidates for radical prostatectomy and pelvic lymph node dissection (PLND). Unfavorable intermediate-risk was defined as having any ≥ 2 intermediate risk factors [T2b-T2c, Gleason score 7, PSA 10-20], Gleason pattern 4+3=7, or ≥ 50% of biopsy cores positive for prostate cancer. High or very high-risk was defined as having T3 or T4 disease, Gleason score ≥8, primary Gleason pattern 5, and/or PSA >20.

All patients received a single dose of POSLUMA with an administered radioactivity (mean ± SD) of 307 ± 23 MBq (8.3 ± 0.62 mCi), followed by PET/CT scan from mid-thigh to base of the skull. Three central readers blinded to clinical information independently interpreted each scan for lesions considered positive for prostate cancer in pelvic lymph nodes, categorized by subregion and left and right laterality [see Dosage and Administration (2.5)] . Positive lesions in the prostate gland, lymph nodes outside the pelvis, soft tissue/parenchyma, and bones were also recorded.

A total of 296 patients (83%) underwent standard-of-care prostatectomy and template PLND and had sufficient histopathology data for evaluation of the pelvic lymph nodes. The mean age was 65 years (range 46 to 82 years); distribution by race was 82% White, 8% Black or African American, 0.3% other, and 10% unreported; and distribution by ethnicity was 5% Hispanic/Latino, 86% non-Hispanic/Latino, and 9% unreported. The median serum PSA was 8.4 ng/mL. The total Gleason score was 7 for 45%, 8 for 26%, and 9 for 25% of the patients, with the remainder of the patients having Gleason scores of 6 or 10. Approximately 24% of patients had pelvic lymph node metastases based on histopathology.

POSLUMA performance was evaluated against histopathology after matching by hemipelvis. Table 6 shows the results, such that at least one true positive hemipelvis region defined a true positive patient.

Table 6: Patient-Level, Hemipelvis Region-Matched Performance of POSLUMA PET for Detection of Pelvic Lymph Node Metastasis (N1) in LIGHTHOUSE
N=296 | Reader 1 | Reader 2 | Reader 3
True Positive | 21 | 19 | 16
False Positive | 16 | 14 | 7
True Negative | 210 | 212 | 219
False Negative | 49 | 51 | 54
Sensitivity, (%) [95% CI] | 30% [20, 42] | 27% [17, 39] | 23% [14, 35]
Specificity, (%) [95% CI] | 93% [89, 96] | 94% [90, 97] | 97% [94, 99]
Positive Predictive Value, (%) [95% CI] | 57% [40, 73] | 58% [39, 75] | 70% [47, 87]
Negative Predictive Value, (%) [95% CI] | 81% [76, 86] | 81% [75, 85] | 80% [75, 85]
CI= confidence interval

In exploratory analyses, there were numerical trends towards higher sensitivity among patients with PSA greater than or equal to the median value (8.4 ng/mL) and among patients with high-risk or very high-risk categorization.

POSLUMA-positive lesions outside of the prostate gland and pelvic lymph nodes (M1) were also evaluated. As a percentage of the 352 patients with an evaluable POSLUMA scan and of the 61 patients with at least one POSLUMA positive M1 lesion, 10% (95% CI: 7% to 13%) and 56% (95% CI: 42% to 68%), respectively, had at least one matching positive M1 lesion between the POSLUMA majority read and a reference standard consisting of other imaging evaluated by a separate consensus panel or histopathology.

14.2 Imaging for Suspected Recurrence of Prostate Cancer

The safety and efficacy of POSLUMA were evaluated in SPOTLIGHT (NCT04186845), a prospective, multicenter, open-label, single-arm study in patients with biochemical evidence of recurrent prostate cancer.

The study enrolled 391 patients with suspected recurrence defined by either serum PSA of at least 0.2 ng/mL after radical prostatectomy (with confirmatory PSA level also at least 0.2 ng/mL) or by an increase in serum PSA of at least 2 ng/mL above the nadir after other therapies.

All patients received a single dose of POSLUMA with an administered radioactivity (mean ± SD) of 306 ± 22 MBq (8.27 ±0.61 mCi), followed by PET/CT scan from mid-thigh to base of the skull. Three central readers blinded to clinical information independently interpreted each scan by region for the presence and location of lesions considered positive for prostate cancer [see Dosage and Administration (2.5)] . The regions interpreted were grouped into three for primary analysis: prostate/prostate bed; pelvic lymph nodes; and other (including extra-pelvic lymph nodes, bone, and soft tissue/parenchyma).

A total of 389 patients had an evaluable POSLUMA PET scan. The mean age was 68 years (range: 43 to 86 years); distribution by race was 75% White, 16% Black or African American, 4% other, and 5% unreported; and distribution by ethnicity 5% was Hispanic/Latino, 87% non-Hispanic/Latino, and 8% unreported. The median baseline serum PSA level was 1.1 ng/mL with 60% of patients having a baseline PSA <2.0 ng/mL. Prior treatment included radical prostatectomy in 79% of the patients.

POSLUMA-positive interpretations were compared to a reference standard of either histopathology or other imaging (CT, MRI, Technetium 99m bone scan, or fluciclovine F 18 PET) obtained within 90 days of the POSLUMA scan using a lesion-to-lesion co-localization method and separate consensus panel. Reference standard information for negative interpretations was not collected.

At least one POSLUMA-positive lesion was detected by at least one reader in 366 patients (94%). Reference standard information consisted of imaging only (n=297) or histopathology (n=69). As a percentage of patients with an evaluable scan, 51% (95% CI: 46% to 56%) for reader 1, 48% (95% CI: 43% to 53%) for reader 2, and 49% (95% CI: 44% to 54%) for reader 3 had at least one matching positive region between the POSLUMA scan and the reference standard. Of all POSLUMA-positive regions, 46% (95% CI: 42% to 50%) for reader 1, 60% (95% CI: 55% to 66%) for reader 2, and 53% (95% CI: 48% to 58%) for reader 3 were categorized as positive by the reference standard.

Table 7 shows patient-level results from the majority read stratified by serum PSA level. Percent PET positivity was calculated as the percentage of patients with POSLUMA-positive lesions out of all patients with an evaluable PET scan. Percent PET positivity includes true and false positives and is not a measure of diagnostic performance.

Table 7: Patient-Level POSLUMA PET Results and Percent PET Positivity Stratified by Serum PSA Level in SPOTLIGHT by Majority Read (N=389)
PSA (ng/mL) | N | PET Positive Patients |  |  |  |  | PET Negative Patients | Percent PET Positivity [95% CI]
PSA (ng/mL) | N | Total | Histopathology |  | Imaging onlya |  | PET Negative Patients | Percent PET Positivity [95% CI]
PSA (ng/mL) | N | Total | PA | NPA | PA | NPA | PET Negative Patients | Percent PET Positivity [95% CI]
< 0.5 | 121 | 77 | 6 | 4 | 27 | 40 | 44 | 64% [54,72]
≥ 0.5 and < 1 | 67 | 51 | 7 | 3 | 24 | 17 | 16 | 76% [64,86]
≥ 1 and < 2 | 45 | 42 | 10 | 2 | 18 | 12 | 3 | 93% [82, 99]
≥ 2 | 156 | 152 | 33 | 3 | 84 | 32 | 4 | 97% [94, 99]
Total | 389 | 322 | 56 | 12 | 153 | 101 | 67 | 83% [79, 86]
PSA = prostate-specific antigen, PA = positive agreement, NPA = no positive agreement, CI = confidence interval
aImaging comprised of one or more of the following: CT, MRI,99mTc Bone Scan, fluciclovine F 18 PET

Variable Interpretation in Patients with Suspected Prostate Cancer Recurrence

POSLUMA reader agreement was evaluated for the three central readers and 389 patients. Inter-reader Fleiss ϰ was 0.41 (95% CI: 0.39-0.43). The three readers agreed on the presence or absence of positive lesions across all five evaluated regions in 118 patients (30% unanimity) [see Warning and Precautions (5.1)].

Given the level of inter-reader agreement observed overall, POSLUMA reader agreement was further evaluated by regional subgroup. The Fleiss ϰ for was 0.40 (95% CI: 0.33-0.46) in the prostate/prostate bed, 0.73 (95% CI: 0.67-0.78) in the pelvic lymph nodes, and 0.62 (95% CI: 0.58-0.65) across the other regions.

16 HOW SUPPLIED/STORAGE AND HANDLING

How Supplied

POSLUMA injection is supplied as a clear, colorless solution in a multiple-dose glass vial (NDC 69932-002-50) containing 296 MBq/mL to 5,846 MBq/mL (8 mCi/mL to 158 mCi/mL) as flotufolastat F 18 gallium in approximately 25 mL at end of synthesis.

Storage and Handling

Store POSLUMA at 20°C to 25°C (68°F to 77°F) [see USP Controlled Room Temperature]. Store POSLUMA in the original container in radiation shielding. The expiration date and time are provided on the container label. Use POSLUMA within 10 hours from end of synthesis.

Dispose of unused POSLUMA in compliance with applicable regulations.

This preparation is approved for use by persons under license by the Nuclear Regulatory Commission or the relevant regulatory authority of an Agreement State.

17 PATIENT COUNSELING INFORMATION

Adequate Hydration

Instruct patients to drink a sufficient amount of water to ensure adequate hydration before their PET study and urge them to drink and urinate as often as possible during the first hours following the administration of POSLUMA, in order to reduce radiation exposure [see Dosage and Administration (2.3) and Warnings and Precautions (5.2)].

Marketed by Blue Earth Diagnostics Ltd., Oxford, OX4 4GA, UK
POSLUMA® is a registered trademark of Blue Earth Diagnostics Ltd.
© 2023 Blue Earth Diagnostics Ltd. – all rights reserved.

Principal Display Panel – 50 mL Vial Label

Sterile

Posluma®

Non-pyrogenic

(flotufolastat F 18) Injection

296 MBq/mL to 5,846 MBq/mL
(8 mCi/mL to 158 mCi/mL) at End of Synthesis (EOS)

Diagnostic - For Intravenous Use Only

Expires 10 hours after EOS